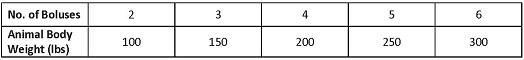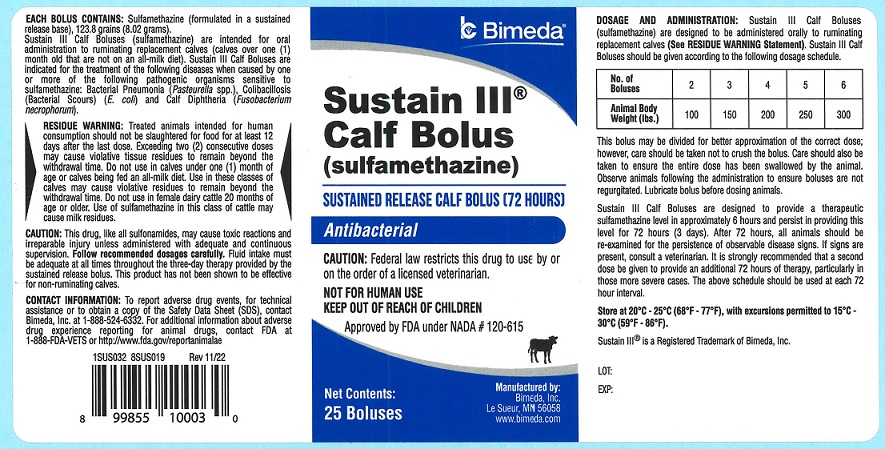 DRUG LABEL: Sustain III Calf
NDC: 61133-1333 | Form: TABLET, EXTENDED RELEASE
Manufacturer: Bimeda, Inc.
Category: animal | Type: PRESCRIPTION ANIMAL DRUG LABEL
Date: 20241211

ACTIVE INGREDIENTS: Sulfamethazine 8.02 g/8.63 g

DESCRIPTION

Sustain III® Calf Bolus (sulfamethazine)

SUSTAINED RELEASED BOLUS (72 HOURS) Antibacterial

CAUTION: Federal law restricts this drug to use by or on the order of a licensed veterinarian.

NOT FOR HUMAN USE

KEEP OUT OF REACH OF CHILDREN

Approved by FDA under NADA # 120-615

INDICATIONS AND USAGE

EACH BOLUS CONTAINS: Sulfamethazine (formulated in a sustained release base), 123.8 grains (8.02 grams).

Sustain III Calf Boluses (sulfamethazine) are intended for oral administration to ruminating replacement calves (calves over one (1) month old that are not on an all-milk diet).

Sustain III Calf Boluses are indicated for the treatment of the following diseases when caused by one or more of the following pathogenic organisms sensitive to sulfamethazine: Bacterial Pneumonia (Pasteurella spp.), Colibacillosis (Bacterial Scours) (E. coli) and Calf Diphtheria (Fusobacteriulm necrophorum).

WARNINGS

RESIDUE WARNING: Treated animals intended for human consumption should not be slaughtered for food for at least 12 days after the last dose. Exceeding two (2) consecutive doses may cause violative tissue residues to remain beyond the withdrawal time. Do not use in calves under one (1) month of age or calves being fed an all-milk diet. Use in these classes of calves may cause violative residues to remain beyond the withdrawal time. Do not use in female dairy cattle 20 months of age or older. Use of sulfamethazine in this class of cattle may cause milk residues.

PRECAUTIONS

CAUTION: This drug, like all sulfonamides, may cause toxic reactions and irreparable injury unless administered with adequate and continuous supervision. Follow recommended dosages carefully. Fluid intake must be adequate at all times throughout the three-day therapy provided by the sustained release bolus. This product has not been shown to be effective for non-ruminating calves.

CONTACT INFORMATION: To report adverse drug events, for technical assistance or to obtain a copy of the Safety Data Sheet (SDS), contact Bimeda, Inc. at 1-888-524-6332. For additional information about adverse drug experience reporting for animal drugs, contact FDA at 1-888-FDA-VETS or http://www.fda.gov/reportanimalae

DOSAGE AND ADMINISTRATION: Sustain III Calf Boluses (sulfamethazine) are designed to be administered orally to ruminating replacement calves (See RESIDUE WARNING Statement). Sustain II Calf Boluses should be given according to the following dosage schedule.

This bolus may be divided for better approximation of the correct dose; however, care should be taken not to crush the bolus. Care should also be taken to ensure the entire dose has been swallowed by the animal. Observe animals following the administration to ensure boluses are not regurgitated. Lubricate bolus before dosing animals.

Sustain III Calf Boluses are designed to provide a therapeutic sulfamethazine level in approximately 6 hours, and persist in providing this level for 72 hours (3 days). After 72 hours, all animals should be re-examined for persistence of observable disease signs. If signs are present, consult a veterinarian. It is strongly recommended that a second dose be given to provide an additional 72 hours of therapy, particularly in those more severe cases. The above schedule should be used at each 72-hour interval.

STORAGE AND HANDLING

Store at 20°C - 25°C (68°F - 77°F), with excursions permitted to 15°C - 30°C (59°F - 86°F).